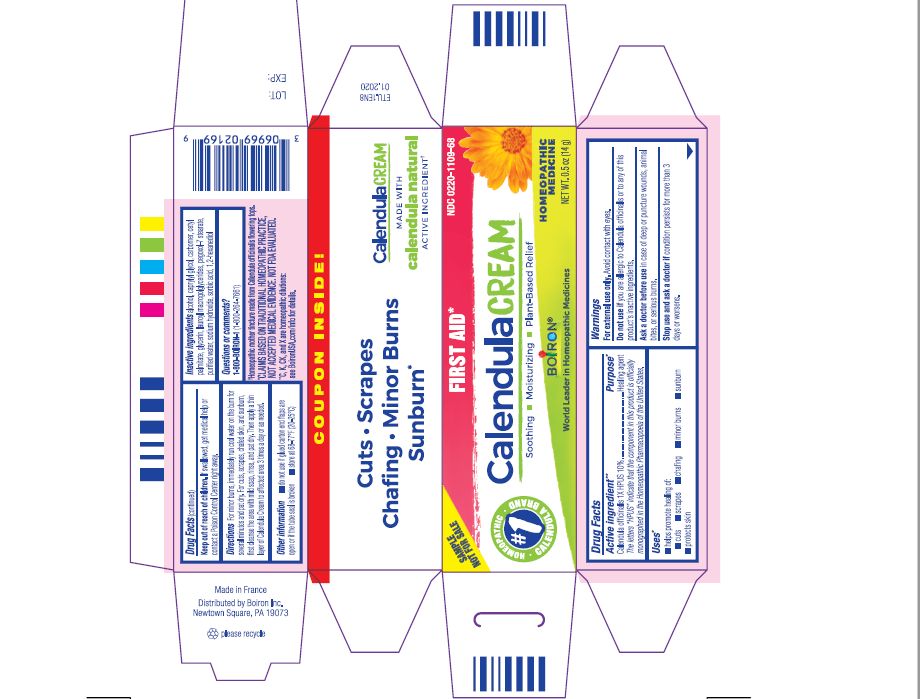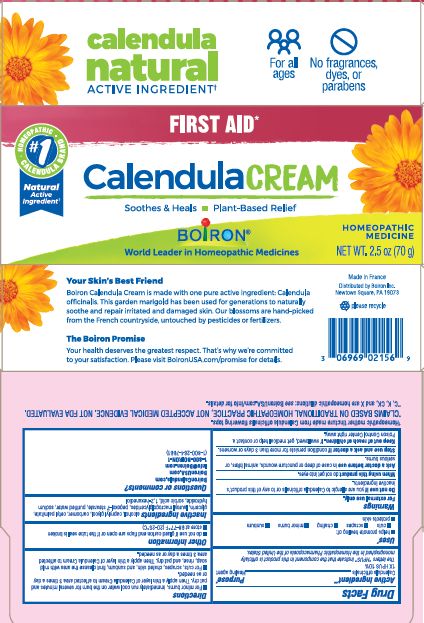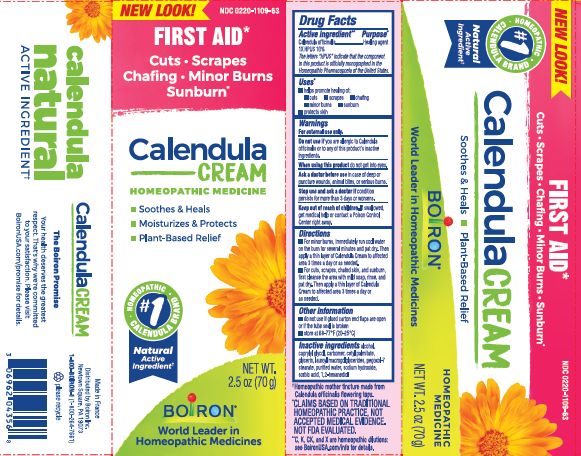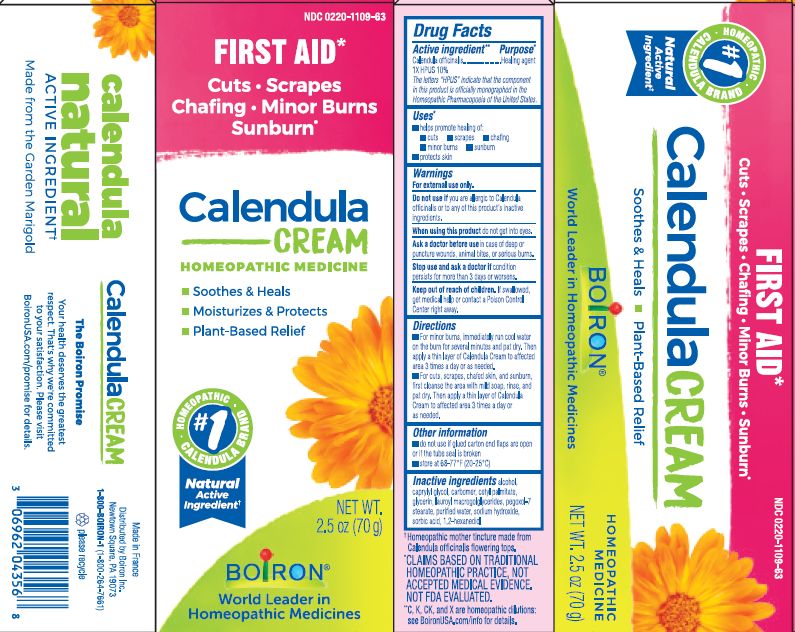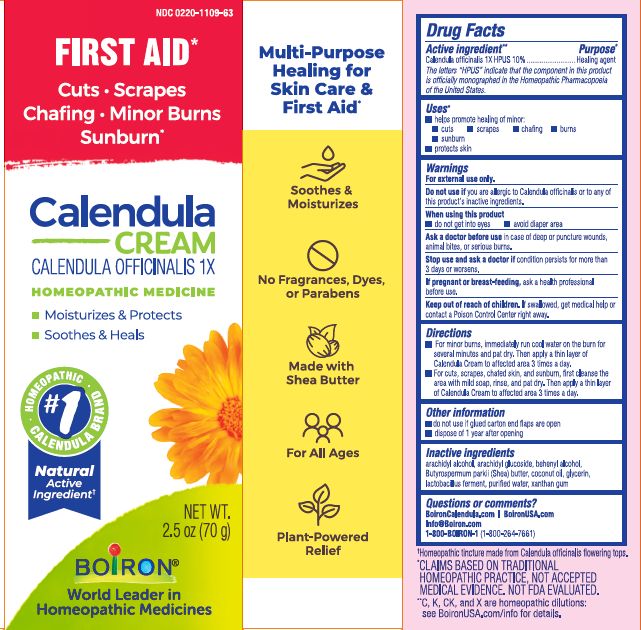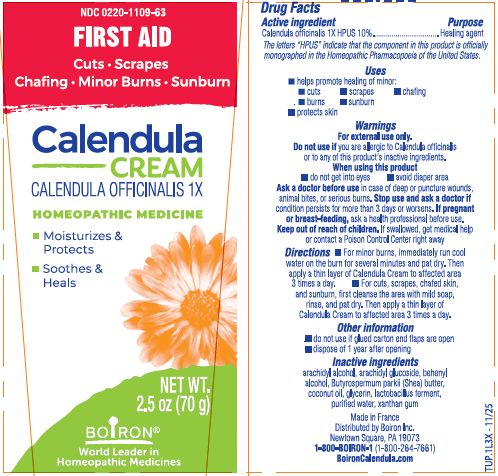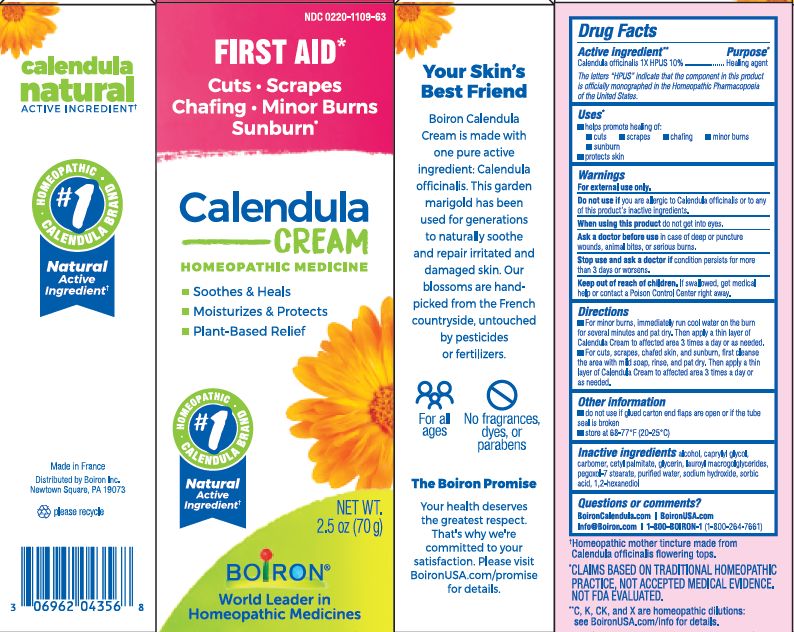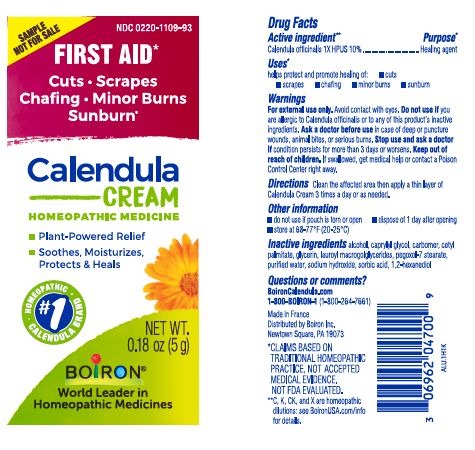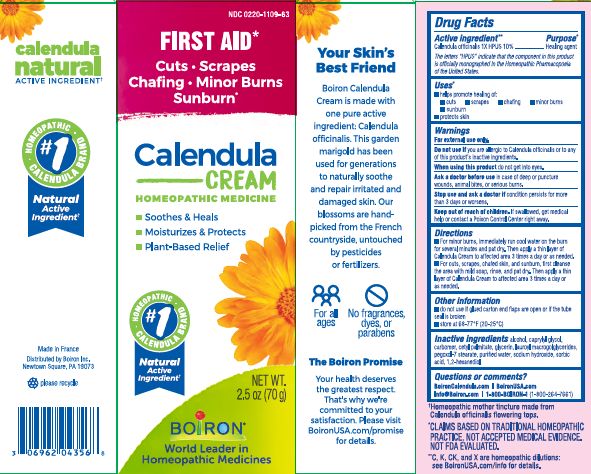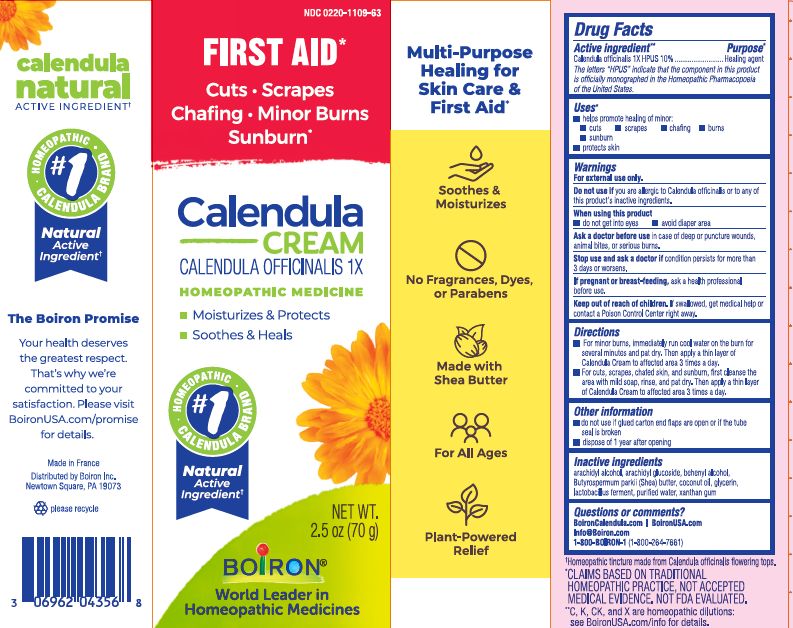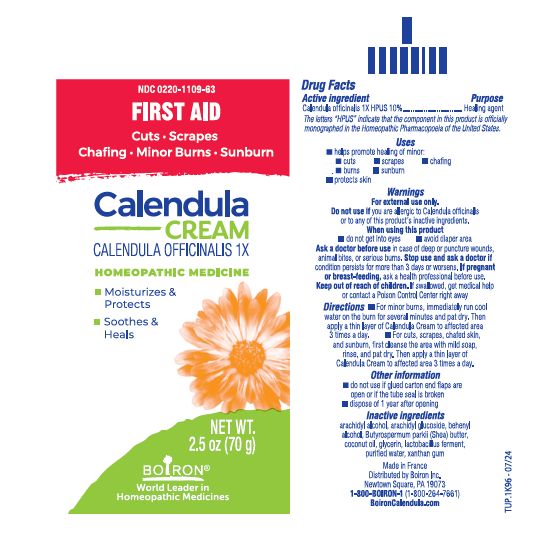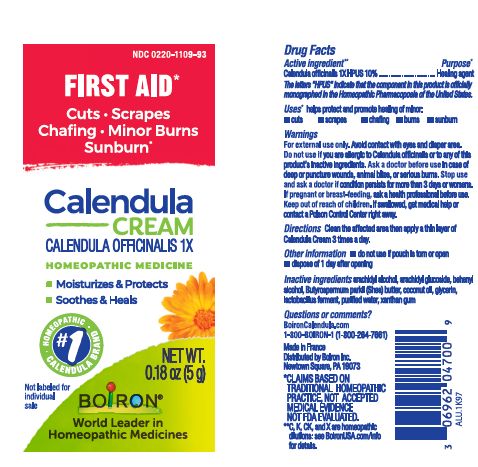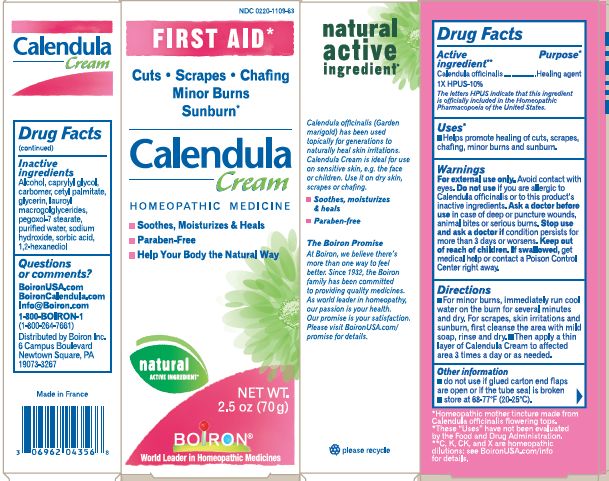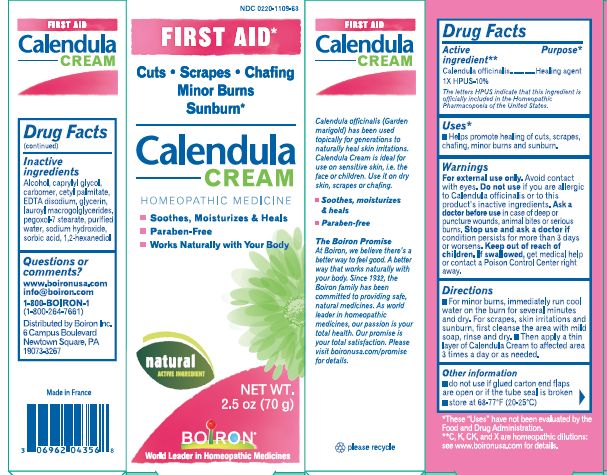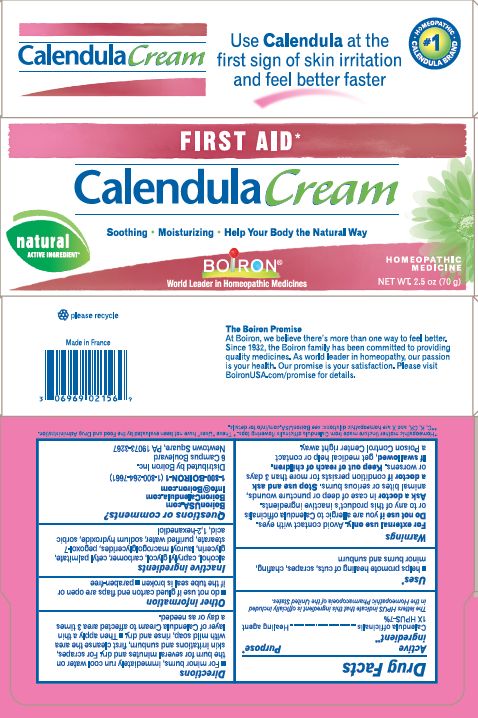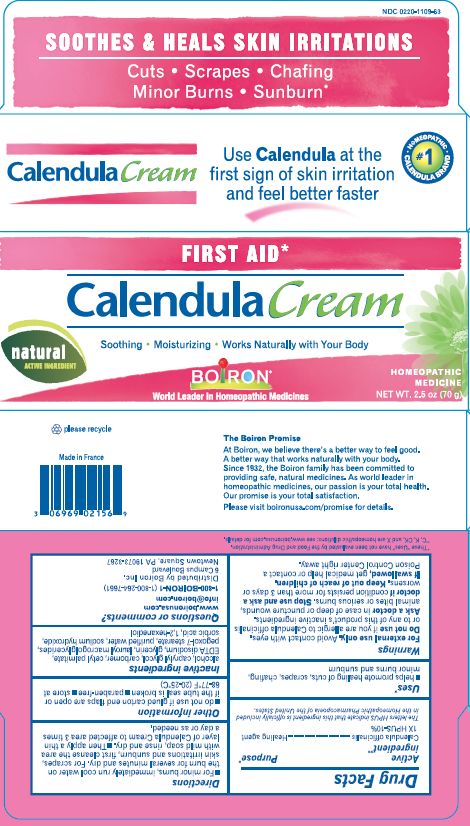 DRUG LABEL: Calendula
NDC: 0220-1109 | Form: CREAM
Manufacturer: Laboratoires Boiron
Category: homeopathic | Type: HUMAN OTC DRUG LABEL
Date: 20251209

ACTIVE INGREDIENTS: CALENDULA OFFICINALIS FLOWERING TOP 1 [hp_X]/1 g
INACTIVE INGREDIENTS: ARACHIDYL ALCOHOL; XANTHAN GUM; BUTYROSPERMUM PARKII (SHEA) BUTTER UNSAPONIFIABLES; GLYCERIN; WATER; DOCOSANOL; ARACHIDYL GLUCOSIDE; COCONUT OIL; LIMOSILACTOBACILLUS FERMENTUM

Calendula Cream 2.5oz, 0.5oz, 0.18oz

Active ingredient**

Calendula officinalis 1X HPUS 10%

The letters "HPUS" indicate that the components in this product are officially monographed in the Homeopathic Pharmacopoeia of the United States.

Purpose*

Calendula officinalis 1X HPUS 10% ... Healing agent

INDICATIONS AND USAGE

- helps promote healing of minor:
- cuts
- scrapes
- chafing
- burns
- sunburn
- protects skin

WARNINGS

For external use only.

Do not use if you are allergic to Calendula officinalis or to any of the product's inactive ingredients.

When using this product

- do not get into eyes
- avoid diaper area

Ask a doctor before use in case of deep or puncture wounds, animal bites, or serious burns.

Stop use and ask doctor if condition persists for more than 3 days or worsens.

PREGNANCY OR BREAST FEEDING

If pregnant or breast-feeding, ask a health professional before use.

Keep out of reach of children. If swallowed, get medical help or contact a Poison Control Center right away.

DOSAGE AND ADMINISTRATION

For minor burns, immediately run cool water on the burn for several minutes and pat dry. Then apply a thin layer of Calendula Cream to affected area 3 times a day.

For cuts, scrapes, chafed skin, and sunburn, first cleanse the area with mild soap, rinse, and pat dry. Then apply a thin layer of Calendula Cream to affected area 3 times a day.

INACTIVE INGREDIENT

arachidyl alcohol, arachidyl glucoside, behenyl alcohol, Butyrospermum parkii (Shea) butter, coconut oil, glycerin, lactobacillus ferment, purified water, xanthan gum

Questions, Comments?

BoironCalendula.com BoironUSA.com

Info@Boiron.com

1-800-BOIRON-1 (1-800-264-7661)
Made in France
Distributed by Boiron, Inc.
Newtown Square, PA 19073

do not use if pouch is torn or open

dispose of 1 day after opening (0.18 oz / 5g)

do not use if glued carton end flaps are open

dispose of 1 day after opening (2.6 OZ / 70 G)

Pouch 0.18 OZ (5g)

Tube 2.6 OZ (70 G)

Tube 0.5 OZ (14 G)

FIRST AID*

Cuts Scrapes Minor Burns Sunburn*

Homeopathic mother tincture made from Calendula officinalis flowering tops.

*CLAIMS BASED ON TRADITIONAL HOMEOPATHIC PRACTICE, NOT ACCEPTED MEDICAL EVIDENCE. NOT FDA EVALUATED.
**C,K,CK, and X are homeopathic dilutions: see BoironUSA.com/info for details.